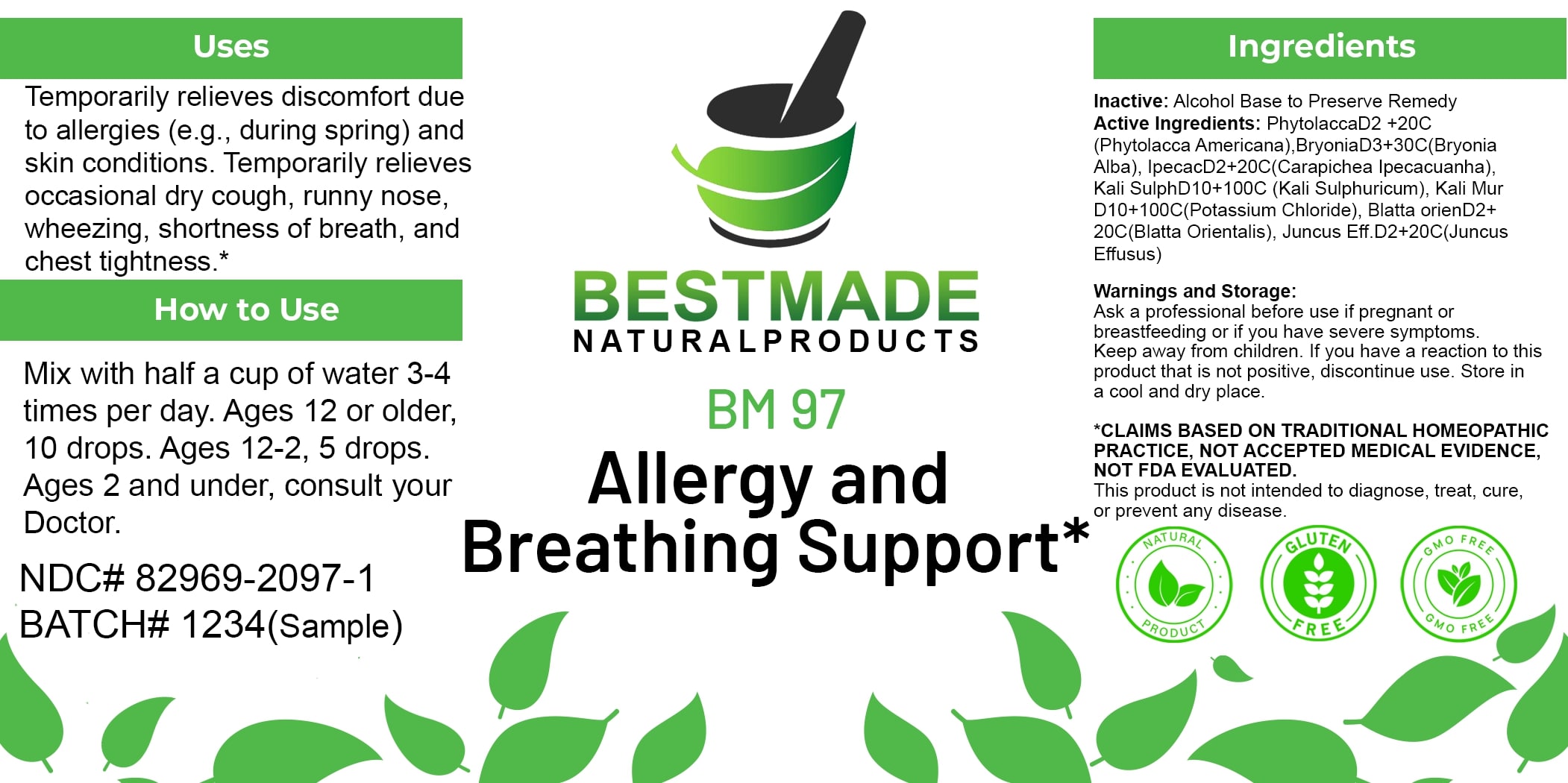 DRUG LABEL: Bestmade Natural Products BM97
NDC: 82969-2097 | Form: LIQUID
Manufacturer: Bestmade Natural Products
Category: homeopathic | Type: HUMAN OTC DRUG LABEL
Date: 20250205

ACTIVE INGREDIENTS: PHYTOLACCA AMERICANA ROOT 30 [hp_C]/30 [hp_C]; BRYONIA ALBA ROOT 30 [hp_C]/30 [hp_C]; POTASSIUM CHLORIDE 30 [hp_C]/30 [hp_C]; JUNCUS EFFUSUS ROOT 30 [hp_C]/30 [hp_C]; POTASSIUM SULFATE 30 [hp_C]/30 [hp_C]; BLATTA ORIENTALIS 30 [hp_C]/30 [hp_C]; IPECAC 30 [hp_C]/30 [hp_C]
INACTIVE INGREDIENTS: ALCOHOL 30 [hp_C]/30 [hp_C]

BM97

DOSAGE AND ADMINISTRATION

How to Use

Mix with half a cup of water 3-4 times per day. Ages 12 or older, 10 drops. Ages 12-2, 5 drops. Ages 2 and under, consult your Doctor.

INACTIVE INGREDIENT

Ingredients

Inactive: Alcohol Base to Preserve Remedy

ACTIVE INGREDIENT

Active Ingredients: Phytolacca D2 + 20C (Phytolacca Americana), Bryonia D3+30C (Bryonia Alba), Ipecac D2+20C (Carapichea Ipecacuanha), Kali Sulph D10+100C (Kali Sulphuricum), Kali Mur D10+100C (Potassium Chloride), Blatta orient D2+ 20C (Blatta Orientalis), Juncus Eff D2+20C (Juncus Effusus)

Uses

Temporarily relieves discomfort due to allergies (e.g., during spring) and skin conditions. Temporarily relieves occasional dry cough, runny nose, wheezing, shortness of breath, and chest tightness.*

*CLAIMS BASED ON TRADITIONAL HOMEOPATHIC PRACTICE, NOT ACCEPTED MEDICAL EVIDENCE. NOT FDA EVALUATED.

This product is not intended to diagnose, treat, cure, or prevent any disease.

Uses

Temporarily relieves discomfort due to allergies (e.g., during spring) and skin conditions. Temporarily relieves occasional dry cough, runny nose, wheezing, shortness of breath, and chest tightness.*

*CLAIMS BASED ON TRADITIONAL HOMEOPATHIC PRACTICE, NOT ACCEPTED MEDICAL EVIDENCE. NOT FDA EVALUATED.

This product is not intended to diagnose, treat, cure, or prevent any disease.

KEEP OUT OF REACH OF CHILDREN

Warnings and Storage:

Ask a professional before use if pregnant or breastfeeding or if you have severe symptoms. Keep away from children. If you have a reaction to this product that is not positive, discontinue use. Store in a cool and dry place.

Warnings and Storage:

Ask a professional before use if pregnant or breastfeeding or if you have severe symptoms. Keep away from children. If you have a reaction to this product that is not positive, discontinue use. Store in a cool and dry place.

*CLAIMS BASED ON TRADITIONAL HOMEOPATHIC PRACTICE, NOT ACCEPTED MEDICAL EVIDENCE. NOT FDA EVALUATED.

This product is not intended to diagnose, treat, cure, or prevent any disease.

Entire package label